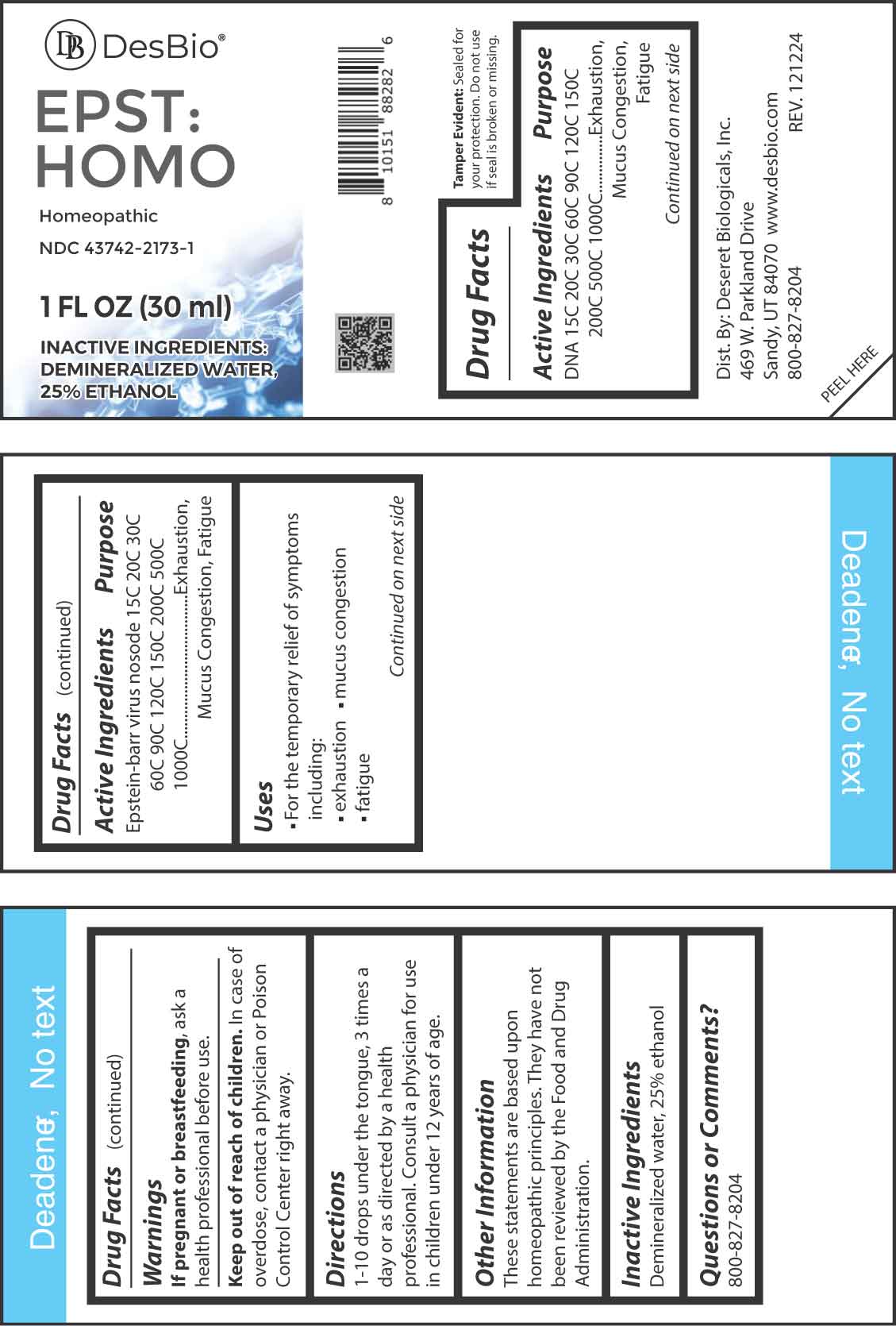 DRUG LABEL: EPST HOMO
NDC: 43742-2173 | Form: LIQUID
Manufacturer: Deseret Biologicals, Inc.
Category: homeopathic | Type: HUMAN OTC DRUG LABEL
Date: 20250408

ACTIVE INGREDIENTS: HERRING SPERM DNA 15 [hp_C]/1 mL; HUMAN HERPESVIRUS 4 15 [hp_C]/1 mL
INACTIVE INGREDIENTS: WATER; ALCOHOL

DRUG FACTS:

ACTIVE INGREDIENT:

DNA 15C, 20C, 30C, 60C, 90C, 120C, 150C, 200C, 500C, 1000C, Epstein-Barr Virus Nosode 15C, 20C, 30C, 60C, 90C, 120C, 150C, 200C, 500C, 1000C.

PURPOSE:

DNA - Exhaustion, Mucus Congestion, Fatigue, Epstein-Barr Virus Nosode - Exhaustion, Mucus Congestion, Fatigue

USES:

• For the temporary relief of symptoms including:

• exhaustion • mucus congestion • fatigue

These statements are based upon homeopathic principles. They have not been reviewed by the Food and Drug Administration.

WARNINGS:

If pregnant or breastfeeding, ask a health professional before use.

Keep out of reach of children. In case of overdose, contact a physician or Poison Control Center right away.

Tamper Evident: Sealed for your protection. Do not use if seal is broken or missing.

KEEP OUT OF REACH OF CHILDREN:

In case of overdose, contact a physician or Poison Control Center right away.

DIRECTIONS:

1-10 drops under the tongue, 3 times a day or as directed by a health professional. Consult a physician for use in children under 12 years of age.

INACTIVE INGREDIENTS:

Demineralized water, 25% ethanol

QUESTIONS:

Dist. By: Deseret Biologicals, Inc.
469 W. Parkland Drive
Sandy, UT 84070

www.desbio.com

800-827-8204

PACKAGE LABEL DISPLAY:

DesBio

EPST:HOMO

Homeopathic

NDC 43742-2173-1

1 FL OZ (30 ml)